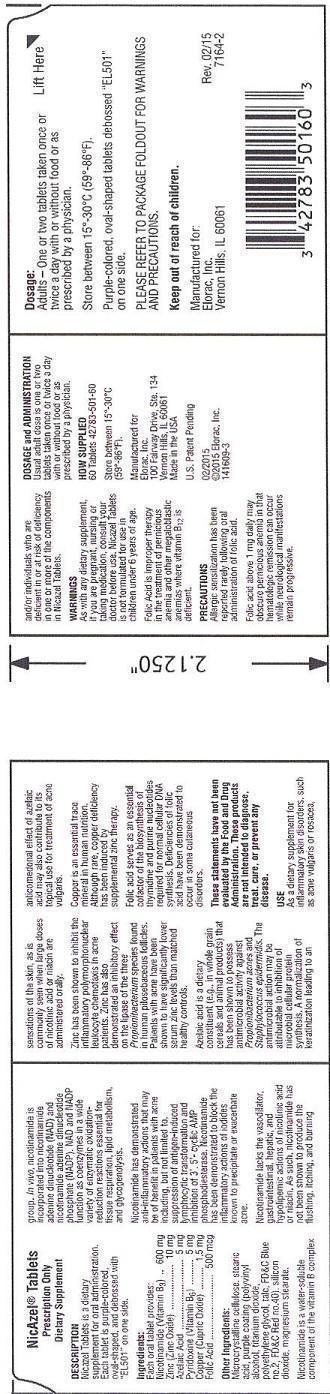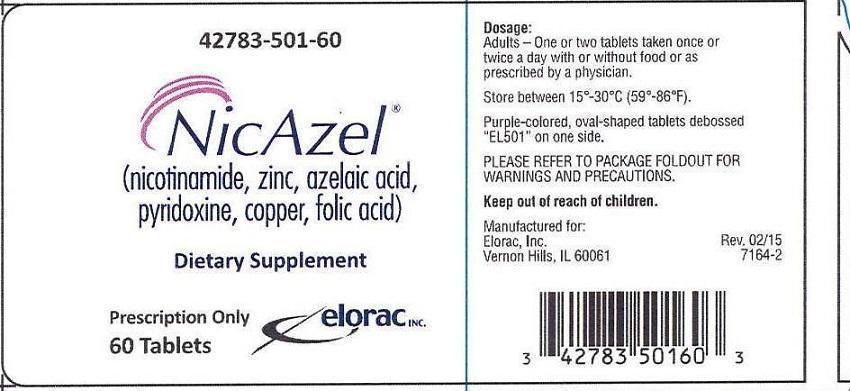 DRUG LABEL: NicAzel
NDC: 42783-501 | Form: TABLET, COATED
Manufacturer: Elorac, Inc
Category: other | Type: DIETARY SUPPLEMENT
Date: 20211208

ACTIVE INGREDIENTS: NIACINAMIDE 600 mg/1 1; ZINC 10 mg/1 1; AZELAIC ACID 5 mg/1 1; PYRIDOXINE 5 mg/1 1; COPPER 1.5 mg/1 1; FOLIC ACID 500 ug/1 1
INACTIVE INGREDIENTS: CELLULOSE, MICROCRYSTALLINE; POLYVINYL ALCOHOL; TITANIUM DIOXIDE; POLYETHYLENE GLYCOL, UNSPECIFIED; TALC; FD&C BLUE NO. 2; FD&C RED NO. 40; SILICON DIOXIDE; MAGNESIUM STEARATE

NicAzel®
Dietary Supplement
Prescription Only

NicAzel® (nicotinamide, zinc, azelaic acid, pyridoxine, copper, folic acid)

Prescription Only

Dietary Supplement

DESCRIPTION

Nicazel Tablets is a dietary supplement for oral administration. Each tablet is purple-colored, oval-shaped, and debossed with "EL501" on one side.

Ingredients:

Each oral tablet provides:

Nicotinamide (Vitamin B3).............600 mg
Zinc (Zinc Oxide)...........................10 mg
Azelaic Acid....................................5 mg
Pyridoxine (Vitamin B6)...................5 mg
Copper (Cupric Oxide)..................1.5 mg
Folic Acid....................................500 mcg

Other Ingredients:

Microcrystalline cellulose, stearic acid, purple coating (polyvinyl alcohol, titanium dioxide, polyethylene glycol, talc, FD&C Blue no. 2, FD&C Red no. 40), silicon dioxide, magnesium stearate.

HEALTH CLAIM

Nicotinamide is a water-soluble component of the vitamin B complex group. In vivo, nicotinamide is incorporated into nicotinamide adenine dinucleotide (NAD), and nicotinamide adenine dinucleotide phosphate (NADP). NAD and NADP function as coenzymes in a wide variety of enzymatic oxidation-reduction reactions essential for tissue respiration, lipid metabolism, and glycogenolysis.

Nicotinamide has demonstrated anti-inflammatory actions that may be of benefit in patients with acne including, but not limited to, suppression of antigen-induced lymphocytic transformation and inhibition of 3',5'- cyclic AMP phosphodiesterase. Nicotinamide has been demonstrated to block the inflammatory actions of iodides known to precipitate or exacerbate acne.

Nicotinamide lacks the vasodilator, gastrointestinal, hepatic and hypolipemic actions of nicotinic acid or niacin. As such, nicotinamide has not been shown to produce the flushing, itching and burning sensations of the skin, as is commonly seen when large doses of nicotinic acid or niacin are administered orally.

Zinc has been shown to inhibit the inflammatory polymorphonuclear leukocyte chemotaxis in acne patients. Zinc has also demonstrated an inhibitory effect on the lipase of the three Propionibacterium species found in human pilosebaceous follicles. Patients with acne have been shown to have significantly lower serum zinc levels than matched healthy controls.

Azelaic Acid is a dietary constituent (e.g., in whole grain cereals and animal products) that has been shown to possess antimicrobial activity against Propionibacterium acnes and Staphylococcus epidermidis. The antimicrobial action may be attributable to inhibition of microbial cellular protein synthesis. A normalization of keratinization leading to an anticomedonal effect of azelaic acid may be also contributed to its topical use for treatment of acne vulgaris.

Copper is an essential trace mineral in human nutrition. Although rare, copper deficiency has been induced by supplemental zinc therapy.

Folic acid serves as an essential cofactor of the biosynthesis of thymidine and purine nucleotides required for normal cellular DNA synthesis. Deficiencies of folic acid have been demonstrated to occur in some cutaneous disorders.

These statements have not been evaluated by the Food and Drug Administration. These products are not intended to diagnose, treat, cure, or prevent any disease.

USE

As a dietary supplement for inflammatory skin disorders, such as acne vulgaris or rosacea, and/or individuals who are deficient in or at risk of deficiency in one or more of the components in Nicazel Tablets.

WARNINGS

As with any dietary supplement, if you are pregnant, nursing or taking medication, consult your doctor before use. Nicazel Tablets is not formulated for use in children under 6 years of age.

Folic Acid is improper therapy in the treatment of pernicious anemia and other megaloblastic anemias where vitamin B12 is deficient.

PRECAUTIONS

Allergic sensitization has been reported rarely following oral administration of folic acid.

Folic acid above 1 mg daily may obscure pernicious anemia in that hematologic remission can occur while neurological manifestations remain progressive.

DOSAGE & ADMINISTRATION

Usual Adult dose is one or two tablets taken once or twice a day with or without food or as prescribed by a physician.

HOW SUPPLIED

60 tablets NDC 42783-501-60

Store between 15°-30°C (59°-86°F).

DOSAGE AND ADMINISTRATION

Manufactured for
Elorac, Inc.
100 Fairway Drive, Ste. 134
Vernon Hills, IL 60061
Made in the USA

U.S. Patent Pending

02/2015
©2015 Elorac, Inc.
141609-3

Dosage:

Adults - One or two tablets taken once or twice a day with or without food or as prescribed by a physician.
Store between 15o-30oC (59o-86oF).

Purple-colored, oval-shaped tablets debossed "EL501" on one side.

PLEASE REFER TO PACKAGE FOLDOUT FOR WARNINGS AND PRECAUTIONS.

Keep out of reach of children.

DOSAGE AND ADMINISTRATION

Manufactured for:
Elorac, Inc.
Vernon Hills, IL 60061

Rev. 02/15
7164-2

PACKAGE LABEL

42783-501-60

NicAzel®
(nicotinamide, zinc, azelaic acid, pyridoxine, copper, folic acid)

Dietary Supplement

Prescription Only
60 Tablets